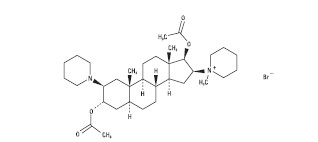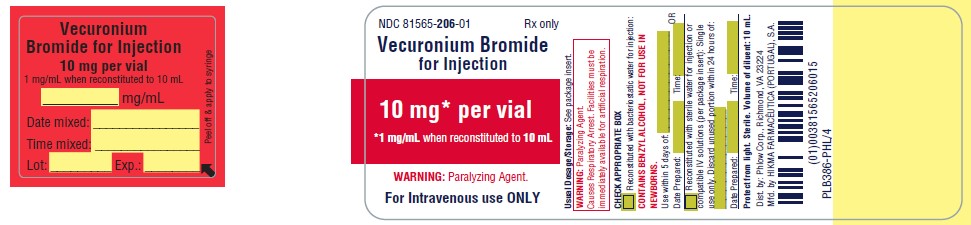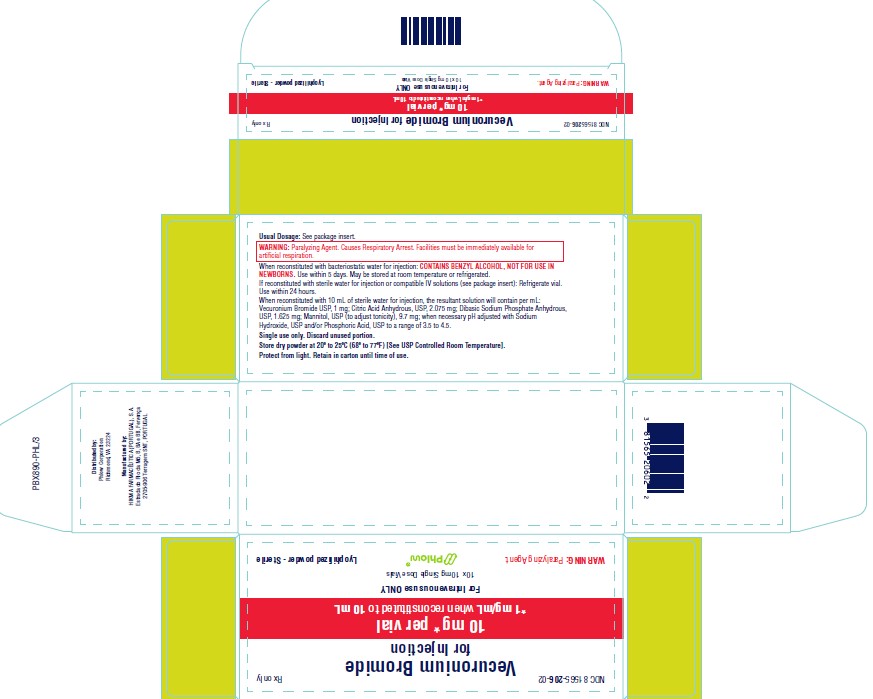 DRUG LABEL: Vecuronium Bromide
NDC: 81565-206 | Form: INJECTION, POWDER, FOR SOLUTION
Manufacturer: Phlow Corp.
Category: prescription | Type: HUMAN PRESCRIPTION DRUG LABEL
Date: 20260227

ACTIVE INGREDIENTS: VECURONIUM BROMIDE 10 mg/1 1
INACTIVE INGREDIENTS: CITRIC ACID ACETATE 20.75 mg/1 1; SODIUM PHOSPHATE 16.25 mg/1 1; MANNITOL 97 mg/1 1; SODIUM HYDROXIDE; PHOSPHORIC ACID

VECURONIUM BROMIDE FOR INJECTION

THIS DRUG SHOULD BE ADMINISTERED BY ADEQUATELY TRAINED INDIVIDUALS FAMILIAR WITH ITS ACTIONS, CHARACTERISTICS, AND HAZARDS.

DESCRIPTION

Vecuronium Bromide for Injection is a nondepolarizing neuromuscular blocking agent of intermediate duration, chemically designated as 1-(3α,17β-Dihydroxy-2β-piperidino-5α-androstan-16β,5α-yl)-1-methylpiperidinium bromide, diacetate. The structural formula is:

Its chemical formula is C34H57BrN2O4 with molecular weight 637.73.

Vecuronium Bromide for Injection is supplied as a sterile nonpyrogenic freeze-dried buffered cake of very fine microscopic crystalline particles for intravenous injection only. Each vial contains 10 mg or 20 mg of vecuronium bromide, USP. In addition, each 10 mg vial contains 20.75 mg citric acid anhydrous, 16.25 mg dibasic sodium phosphate anhydrous, 97 mg mannitol (to adjust tonicity), sodium hydroxide and/or phosphoric acid to buffer and adjust to a pH range of 3.5 to 4.5. Each 20 mg vial contains 41.5 mg citric acid anhydrous, 32.5 mg dibasic sodium phosphate anhydrous, 194 mg mannitol (to adjust tonicity), sodium hydroxide and/or phosphoric acid to buffer and adjust to a pH range of 3.5 to 4.5.

CLINICAL PHARMACOLOGY

Vecuronium is a nondepolarizing neuromuscular blocking agent possessing all of the characteristic pharmacological actions of this class of drugs (curariform). It acts by competing for cholinergic receptors at the motor end-plate. The antagonism to acetylcholine is inhibited and neuromuscular block is reversed by acetylcholinesterase inhibitors such as neostigmine, edrophonium, and pyridostigmine. Vecuronium is about 1/3 more potent than pancuronium; the duration of neuromuscular blockade produced by vecuronium is shorter than that of pancuronium at initially equipotent doses. The time to onset of paralysis decreases and the duration of maximum effect increases with increasing vecuronium doses. The use of a peripheral nerve stimulator is recommended in assessing the degree of muscular relaxation with all neuromuscular blocking drugs. The ED90 (dose required to produce 90% suppression of the muscle twitch response with balanced anesthesia) has averaged 0.057 mg/kg (0.049 to 0.062 mg/kg in various studies). An initial vecuronium bromide dose of 0.08 to 0.1 mg/kg generally produces first depression of twitch in approximately 1 minute, good or excellent intubation conditions within 2.5 to 3 minutes, and maximum neuromuscular blockade within 3 to 5 minutes of injection in most patients.

Under balanced anesthesia, the time to recovery to 25% of control (clinical duration) is approximately 25 to 40 minutes after injection and recovery is usually 95% complete approximately 45 to 65 minutes after injection of intubating dose. The neuromuscular blocking action of vecuronium is slightly enhanced in the presence of potent inhalation anesthetics. If vecuronium is first administered more than 5 minutes after the start of the inhalation of enflurane, isoflurane, or halothane, or when steady state has been achieved, the intubating dose of vecuronium may be decreased by approximately 15% (see DOSAGE AND ADMINISTRATION). Prior administration of succinylcholine may enhance the neuromuscular blocking effect of vecuronium and its duration of action. With succinylcholine as the intubating agent, initial doses of 0.04 to 0.06 mg/kg of vecuronium bromide will produce complete neuromuscular block with clinical duration of action of 25 to 30 minutes. If succinylcholine is used prior to vecuronium, the administration of vecuronium should be delayed until the patient starts recovering from succinylcholine induced neuromuscular blockade. The effect of prior use of other nondepolarizing neuromuscular blocking agents on the activity of vecuronium has not been studied (see PRECAUTIONS, DRUG INTERACTIONS).

Repeated administration of maintenance doses of vecuronium has little or no cumulative effect on the duration of neuromuscular blockade. Therefore, repeat doses can be administered at relatively regular intervals with predictable results. After an initial dose of 0.08 to 0.1 mg/kg under balanced anesthesia, the first maintenance dose (suggested maintenance dose is 0.01 to 0.015 mg/kg) is generally required within 25 to 40 minutes; subsequent maintenance doses, if required, may be administered at approximately 12 to 15 minute intervals. Halothane anesthesia increases the clinical duration of the maintenance dose only slightly. Under enflurane a maintenance dose of 0.01 mg/kg is approximately equal to 0.015 mg/kg dose under balanced anesthesia.

The recovery index (time from 25% to 75% recovery) is approximately 15 to 25 minutes under balanced or halothane anesthesia. When recovery from vecuronium neuromuscular blocking effect begins, it proceeds more rapidly than recovery from pancuronium. Once spontaneous recovery has started, the neuromuscular block produced by vecuronium is readily reversed with various anticholinesterase agents, e.g., pyridostigmine, neostigmine, or edrophonium in conjunction with an anticholinergic agent such as atropine or glycopyrrolate. Rapid recovery is a finding consistent with vecuronium short elimination half-life, although there have been occasional reports of prolonged neuromuscular blockade in patients in the intensive care unit (see PRECAUTIONS, LONG TERM USE IN I.C.U.).

The administration of clinical doses of vecuronium is not characterized by laboratory or clinical signs of chemically mediated histamine release. This does not preclude the possibility of rare hypersensitivity reactions (see ADVERSE REACTIONS).

Pharmacokinetics

At clinical doses of 0.04 to 0.1 mg/kg, 60 to 80% of vecuronium bromide is usually bound to plasma protein. The distribution half-life following a single intravenous dose (range 0.025 to 0.28 mg/kg) is approximately 4 minutes. Elimination half-life over this sample dosage range is approximately 65 to 75 minutes in healthy surgical patients and in renal failure patients undergoing transplant surgery.

In late pregnancy, elimination half-life may be shortened to approximately 35 to 40 minutes. The volume of distribution at steady state is approximately 300 to 400 mL/kg; systemic rate of clearance is approximately 3 to 4.5 mL/kg/minute. In man, urine recovery of vecuronium varies from 3 to 35% within 24 hours. Data derived from patients requiring insertion of a T-tube in the common bile duct suggests that 25 to 50% of a total intravenous dose of vecuronium may be excreted in bile within 42 hours. Only unchanged vecuronium has been detected in human plasma following use during surgery. In addition, one metabolite, 3-desacetyl vecuronium, has been rarely detected in human plasma following prolonged clinical use in the I.C.U. (See PRECAUTIONS: LONG TERM USE IN I.C.U.). The 3-desacetyl vecuronium metabolite has been recovered in the urine of some patients in quantities that account for up to 10% of injected dose; 3-desacetyl vecuronium has also been recovered by T-tube in some patients accounting for up to 25% of the injected dose.

This metabolite has been judged by animal screening (dogs and cats) to have 50% or more of the potency of vecuronium; equipotent doses are of approximately the same duration as vecuronium in dogs and cats. Biliary excretion accounts for about half the dose of vecuronium within 7 hours in the anesthetized rat. Circulatory bypass of the liver (cat preparation) prolongs recovery from vecuronium. Limited data derived from patients with cirrhosis or cholestasis suggests that some measurements of recovery may be doubled in such patients. In patients with renal failure, measurements of recovery do not differ significantly from similar measurements in healthy patients.

Studies involving routine hemodynamic monitoring in good risk surgical patients reveal that the administration of vecuronium in doses up to three times that needed to produce clinical relaxation (0.15 mg/kg) did not produce clinically significant changes in systolic, diastolic or mean arterial pressure. The heart rate, under similar monitoring, remained unchanged in some studies and was lowered by a mean of up to 8% in other studies. A large dose of 0.28 mg/kg administered during a period of no stimulation, while patients were being prepared for coronary artery bypass grafting was not associated with alterations in rate-pressure-product or pulmonary capillary wedge pressure. Systemic vascular resistance was lowered slightly and cardiac output was increased insignificantly. (The drug has not been studied in patients with hemodynamic dysfunction secondary to cardiac valvular disease.) Limited clinical experience with use of vecuronium bromide during the surgery for pheochromocytoma has shown that administration of this drug is not associated with changes in blood pressure or heart rate.

Unlike other nondepolarizing skeletal muscle relaxants, vecuronium has no clinically significant effects on hemodynamic parameters. Vecuronium will not counteract those hemodynamic changes or known side effects produced by or associated with anesthetic agents, other drugs or various other factors known to alter hemodynamics.

INDICATIONS AND USAGE

Vecuronium bromide is indicated as an adjunct to general anesthesia, to facilitate endotracheal intubation and to provide skeletal muscle relaxation during surgery or mechanical ventilation.

CONTRAINDICATIONS

Vecuronium bromide is contraindicated in patients known to have a hypersensitivity to it.

WARNINGS

Anaphylaxis

Severe anaphylactic reactions to neuromuscular blocking agents, including VECURONIUM BROMIDE, have been reported. These reactions have in some cases been life-threatening and fatal. Due to the potential severity of these reactions, the necessary precautions, such as the immediate availability of appropriate emergency treatment, should be taken. Precautions should also be taken in those individuals who have had previous anaphylactic reactions to other neuromuscular blocking agents since cross-reactivity between neuromuscular blocking agents, both depolarizing and non-depolarizing, has been reported in this class of drugs.

VECURONIUM SHOULD BE ADMINISTERED IN CAREFULLY ADJUSTED DOSAGE BY OR UNDER THE SUPERVISION OF EXPERIENCED CLINICIANS WHO ARE FAMILIAR WITH ITS ACTIONS AND THE POSSIBLE COMPLICATIONS THAT MIGHT OCCUR FOLLOWING ITS USE. THE DRUG SHOULD NOT BE ADMINISTERED UNLESS FACILITIES FOR INTUBATION, ARTIFICIAL RESPIRATION, OXYGEN THERAPY, AND REVERSAL AGENTS ARE IMMEDIATELY AVAILABLE. THE CLINICIAN MUST BE PREPARED TO ASSIST OR CONTROL RESPIRATION. TO REDUCE THE POSSIBILITY OF PROLONGED NEUROMUSCULAR BLOCKADE AND OTHER POSSIBLE COMPLICATIONS THAT MIGHT OCCUR FOLLOWING LONG-TERM USE IN THE I.C.U., VECURONIUM OR ANY OTHER NEUROMUSCULAR BLOCKING AGENT SHOULD BE ADMINISTERED IN CAREFULLY ADJUSTED DOSES BY OR UNDER THE SUPERVISION OF EXPERIENCED CLINICIANS WHO ARE FAMILIAR WITH ITS ACTIONS AND WHO ARE FAMILIAR WITH APPROPRIATE PERIPHERAL NERVE STIMULATOR MUSCLE MONITORING TECHNIQUES (see PRECAUTIONS, LONG TERM USE IN I.C.U.).

In patients who are known to have myasthenia gravis or the myasthenic (Eaton-Lambert) syndrome, small doses of vecuronium may have profound effects. In such patients, a peripheral nerve stimulator and use of a small test dose may be of value in monitoring the response to administration of muscle relaxants.

Risk of Death due to Medication Errors

Administration of vecuronium bromide for injection results in paralysis, which may lead to respiratory arrest and death; this progression may be more likely to occur in a patient for whom it is not intended. Confirm proper selection of intended product and avoid confusion with other injectable solutions that are present in critical care and other clinical settings. If another healthcare provider is administering the product, ensure that the intended dose is clearly labeled and communicated.

PRECAUTIONS

Since allergic cross-reactivity has been reported in this class, request information from your patients about previous anaphylactic reactions to other neuromuscular blocking agents. In addition, inform your patients that severe anaphylactic reactions to neuromuscular blocking agents, including VECURONIUM BROMIDE have been reported.

Renal Failure

Vecuronium is well tolerated without clinically significant prolongation of neuromuscular blocking effect in patients with renal failure who have been optimally prepared for surgery by dialysis. Under emergency conditions in anephric patients some prolongation of neuromuscular blockade may occur; therefore, if anephric patients cannot be prepared for non-elective surgery, a lower initial dose of vecuronium should be considered.

Altered Circulation Time

Conditions associated with slower circulation time in cardiovascular disease, old age, edematous states resulting in increased volume of distribution may contribute to delay in onset time, therefore, dosage should not be increased.

Hepatic Disease

Experience in patients with cirrhosis or cholestasis has revealed prolonged recovery time in keeping with the role the liver plays in vecuronium metabolism and excretion (see CLINICAL PHARMACOLOGY, Pharmacokinetics). Data currently available do not permit dosage recommendations in patients with impaired liver function.

Long-term Use in I.C.U.

In the intensive care unit, long-term use of neuromuscular blocking drugs to facilitate mechanical ventilation may be associated with prolonged paralysis and/or skeletal muscle weakness, that may be first noted during attempts to wean such patients from the ventilator. Typically, such patients receive other drugs such as broad spectrum antibiotics, narcotics and/or steroids and may have electrolyte imbalance and diseases which lead to electrolyte imbalance, hypoxic episodes of varying duration, acid-base imbalance and extreme debilitation, any of which may enhance the actions of a neuromuscular blocking agent. Additionally, patients immobilized for extended periods frequently develop symptoms consistent with disuse muscle atrophy. The recovery picture may vary from regaining movement and strength in all muscles to initial recovery of movement of the facial and small muscles of the extremities then to the remaining muscles. In rare cases recovery may be over an extended period of time and may even, on occasion, involve rehabilitation. Therefore, when there is a need for long-term mechanical ventilation, the benefits-to-risk ratio of neuromuscular blockade must be considered.

Continuous infusion or intermittent bolus dosing to support mechanical ventilation, has not been studied sufficiently to support dosage recommendations. IN THE INTENSIVE CARE UNIT, APPROPRIATE MONITORING, WITH THE USE OF A PERIPHERAL NERVE STIMULATOR TO ASSESS THE DEGREE OF NEUROMUSCULAR BLOCKADE IS RECOMMENDED TO HELP PRECLUDE POSSIBLE PROLONGATION OF THE BLOCKADE. WHENEVER THE USE OF VECURONIUM OR ANY NEUROMUSCULAR BLOCKING AGENT IS CONTEMPLATED IN THE I.C.U., IT IS RECOMMENDED THAT NEUROMUSCULAR TRANSMISSION BE MONITORED CONTINUOUSLY DURING ADMINISTRATION AND RECOVERY WITH THE HELP OF A NERVE STIMULATOR. ADDITIONAL DOSES OF VECURONIUM OR ANY OTHER NEUROMUSCULAR BLOCKING AGENT SHOULD NOT BE GIVEN BEFORE THERE IS A DEFINITE RESPONSE TO T1 OR TO THE FIRST TWITCH. IF NO RESPONSE IS ELICITED, INFUSION ADMINISTRATION SHOULD BE DISCONTINUED UNTIL A RESPONSE RETURNS.

Severe Obesity or Neuromuscular Disease

Patients with severe obesity or neuromuscular disease may pose airway and/or ventilatory problems requiring special care before, during and after the use of neuromuscular blocking agents such as vecuronium.

Malignant Hyperthermia

Many drugs used in anesthetic practice are suspected of being capable of triggering a potentially fatal hypermetabolism of skeletal muscle known as malignant hyperthermia. There are insufficient data derived from screening in susceptible animals (swine) to establish whether or not vecuronium is capable of triggering malignant hyperthermia.

C.N.S.

Vecuronium has no known effect on consciousness, the pain threshold or cerebration. Administration must be accompanied by adequate anesthesia or sedation.

Drug Interactions

Prior administration of succinylcholine may enhance the neuromuscular blocking effect of vecuronium and its duration of action. If succinylcholine is used before vecuronium, the administration of vecuronium should be delayed until the succinylcholine effect shows signs of wearing off. With succinylcholine as the intubating agent, initial doses of 0.04 to 0.06 mg/kg of vecuronium may be administered to produce complete neuromuscular block with clinical duration of action of 25 to 30 minutes (see CLINICAL PHARMACOLOGY).

The use of vecuronium before succinylcholine, in order to attenuate some of the side effects of succinylcholine, has not been sufficiently studied.

Other nondepolarizing neuromuscular blocking agents (pancuronium, d-tubocurarine, metocurine, and gallamine) act in the same fashion as does vecuronium, therefore, these drugs and vecuronium, may manifest an additive effect when used together. There are insufficient data to support concomitant use of vecuronium and other competitive muscle relaxants in the same patient.

Inhalational Anesthetics

Use of volatile inhalational anesthetics such as enflurane, isoflurane, and halothane with vecuronium will enhance neuromuscular blockade. Potentiation is most prominent with use of enflurane and isoflurane. With the above agents the initial dose of vecuronium may be the same as the balanced anesthesia unless the inhalational anesthetic has been administered for a sufficient time at a sufficient dose to have reached clinical equilibrium (see CLINICAL PHARMACOLOGY).

Antibiotics

Parenteral/intraperitoneal administration of high doses of certain antibiotics may intensify or produce neuromuscular block on their own. The following antibiotics have been associated with various degrees of paralysis: aminoglycosides (such as neomycin, streptomycin, kanamycin, gentamicin, and dihydrostreptomycin); tetracyclines; bacitracin; polymyxin B; colistin; and sodium colistimethate. If these or other newly introduced antibiotics are used in conjunction with vecuronium, unexpected prolongation of neuromuscular block should be considered a possibility.

Thiopental

Reconstituted vecuronium, which has an acid pH, should not be mixed with alkaline solutions (e.g., barbiturate solutions such as thiopental) in the same syringe or administered simultaneously during intravenous infusion through the same needle or through the same intravenous line (see DOSAGE AND ADMINISTRATION-COMPATIBILITY).

Other

Experience concerning injection of quinidine during recovery from use of other muscle relaxants suggests that recurrent paralysis may occur. This possibility must also be considered for vecuronium. Vecuronium induced neuromuscular blockade has been counteracted by alkalosis and enhanced by acidosis in experimental animals (cat). Electrolyte imbalance and diseases which lead to electrolyte imbalance, such as adrenal cortical insufficiency, have been shown to alter neuromuscular blockade. Depending on the nature of the imbalance, either enhancement or inhibition may be expected. Magnesium salts, administered for the management of toxemia of pregnancy may enhance the neuromuscular blockade.

Drug/Laboratory Test Interactions

None known

Carcinogenesis, Mutagenesis, Impairment of Fertility

Long-term studies in animals have not been performed to evaluate carcinogenic or mutagenic potential or impairment of fertility.

Pregnancy

Teratogenic Effects; Pregnancy Category C:

Animal reproduction studies have not been conducted with vecuronium. It is also not known whether vecuronium can cause fetal harm when administered to a pregnant woman or can affect reproduction capacity. Vecuronium should be given to a pregnant woman only if clearly needed

Labor and Delivery

The use of vecuronium in patients undergoing cesarean section has been reported in the literature. Following tracheal intubation with succinylcholine, vecuronium dosages of 0.04 mg/kg (n=11) and 0.06 to 0.08 mg/kg (n=20) were administered. The umbilical venous plasma concentrations were 11% of maternal concentrations at delivery and mean neonate APGAR scores at 5 minutes were ≥ 9 in both reports. The action of neuromuscular blocking agents may be enhanced by magnesium salts administered for the management of toxemia of pregnancy.

Nursing Mothers

It is not known whether this drug is excreted in human milk. Because many drugs are excreted in human milk, caution should be exercised when vecuronium is administered to a nursing woman.

Pediatric Use

Infants under 1 year of age but older than 7 weeks also tested under halothane anesthesia, are moderately more sensitive to vecuronium on a mg/kg basis than adults and take about 1.5 times as long to recover. See DOSAGE AND ADMINSTRATION: Use in Pediatrics subsection for recommendations for use in pediatric patients 7 weeks to 16 years of age. The safety and effectiveness of vecuronium in pediatric patients less than 7 weeks of age have not been established.

Geriatric Use

Clinical studies of vecuronium did not include sufficient numbers of subjects aged 65 and over to determine whether they respond differently from younger subjects. There are some reports in the peer reviewed literature of increased effect and longer duration of action of vecuronium in the elderly compared to younger patients. However, other reports have found no significant differences between healthy elderly and younger adults. Advanced age or other conditions associated with slower circulation time, may be associated with a delay in onset time (see PRECAUTIONS-ALTERED CIRCULATION TIME). Nevertheless, recommended doses of vecuronium should not be increased in these patients to reduce onset time, as higher doses produce a longer duration of action (see CLINICAL PHARMACOLOGY). Dose selections for an elderly patient should be cautious, usually starting at the low end of the dosing range, reflecting the greater frequency of decreased hepatic, renal, or cardiac function, and of concomitant disease or other drug therapy. Close monitoring of neuromuscular function is recommended

ADVERSE REACTIONS

There have been postmarketing reports of severe allergic reactions (anaphylactic and anaphylactoid reactions) associated with use of neuromuscular blocking agents, including VECURONIUM BROMIDE. These reactions, in some cases, have been life-threatening and fatal. Because these reactions were reported voluntarily from a population of uncertain size, it is not possible to reliably estimate their frequency (See WARNINGS and PRECAUTIONS).

The most frequent adverse reaction to nondepolarizing blocking agents as a class consists of an extension of the drug's pharmacological action beyond the time period needed. This may vary from skeletal muscle weakness to profound and prolonged skeletal muscle paralysis resulting in respiration insufficiency or apnea.

Inadequate reversal of the neuromuscular blockade is possible with vecuronium bromide as with all curariform drugs. These adverse reactions are managed by manual or mechanical ventilation until recovery is judged adequate. Little or no increase in intensity of blockade or duration of action with vecuronium bromide is noted from the use of thiobarbiturates, narcotic analgesics, nitrous oxide, or droperidol. See OVERDOSAGE for discussion of other drugs used in anesthetic practice which also cause respiratory depression.

Prolonged to profound extensions of paralysis and/or muscle weakness as well as muscle atrophy have been reported after long-term use to support mechanical ventilation in the intensive care unit (see PRECAUTIONS, LONG TERM USE IN I.C.U.). The administration of vecuronium bromide has been associated with rare instances of hypersensitivity reactions (bronchospasm, hypotension and/or tachycardia, sometimes associated with acute urticaria or erythema); (see also CLINICAL PHARMACOLOGY).

OVERDOSAGE

The possibility of iatrogenic overdosage can be minimized by carefully monitoring muscle twitch response to peripheral nerve stimulation.

Excessive doses of vecuronium produce enhanced pharmacological effects. Residual neuromuscular blockade beyond the time period needed may occur with vecuronium as with other neuromuscular blockers. This may be manifested by skeletal muscle weakness, decreased respiratory reserve, low tidal volume, or apnea. A peripheral nerve stimulator may be used to assess the degree of residual neuromuscular blockade from other causes of decreased respiratory reserve.

Respiratory depression may be due either wholly or in part to other drugs used during the conduct of general anesthesia such as narcotics, thiobarbiturates and other central nervous system depressants.

Under such circumstances the primary treatment is maintenance of a patent airway and manual or mechanical ventilation until complete recovery of normal respiration is assured. Pyridostigmine, neostigmine, or edrophonium, in conjunction with atropine or glycopyrrolate will usually antagonize the skeletal muscle relaxant action of vecuronium. Satisfactory reversal can be judged by adequacy of skeletal muscle tone and by adequacy of respiration. A peripheral nerve stimulator may also be used to monitor restoration of twitch height. Failure of prompt reversal (within 30 minutes) may occur in the presence of extreme debilitation, carcinomatosis, and with concomitant use of certain broad spectrum antibiotics, or anesthetic agents and other drugs which enhance neuromuscular blockade or cause respiratory depression of their own. Under such circumstances the management is the same as that of prolonged neuromuscular blockade. Ventilation must be supported by artificial means until the patient has resumed control of his respiration. Prior to the use of reversal agents, reference should be made to the specific package insert of the reversal agent.

The effects of hemodialysis and peritoneal dialysis on plasma levels of vecuronium and its metabolite are unknown.

DOSAGE AND ADMINISTRATION

Vecuronium bromide for injection is for intravenous use only.

This drug should be administered by or under the supervision of experienced clinicians familiar with the use of neuromuscular blocking agents. Dosage must be individualized in each case. The dosage information which follows is derived from studies based upon units of drug per unit of body weight and is intended to serve as a guide only, especially regarding enhancement of neuromuscular blockade of vecuronium bromide by volatile anesthetics and by prior use of succinylcholine (see PRECAUTIONS: DRUG INTERACTIONS).

To obtain maximum clinical benefits of vecuronium bromide and to minimize the possibility of overdosage, the monitoring of muscle twitch response to peripheral nerve stimulation is advised.

The recommended initial dose of vecuronium bromide is 0.08 to 0.1 mg/kg (1.4 to 1.75 times the ED90) given as an intravenous bolus injection. This dose can be expected to produce good or excellent non-emergency intubation conditions in 2.5 to 3 minutes after injection. Under balanced anesthesia, clinically required neuromuscular blockade lasts approximately 25 to 30 minutes, with recovery to 25% of control achieved approximately 25 to 40 minutes after injection and recovery to 95% of control achieved approximately 45 to 65 minutes after injection. In the presence of potent inhalation anesthetics, the neuromuscular blocking effect of vecuronium bromide is enhanced. If vecuronium bromide is first administered more than 5 minutes after the start of inhalation agent or when steady-state has been achieved, the initial vecuronium bromide dose may be reduced by approximately 15%, i.e., 0.06 to 0.085 mg/kg.

Prior administration of succinylcholine may enhance the neuromuscular blocking effect and duration of action of vecuronium bromide. If intubation is performed using succinylcholine, a reduction of initial dose of vecuronium bromide to 0.04 to 0.06 mg/kg with inhalation anesthesia and 0.05 to 0.06 mg/kg with balanced anesthesia may be required.

During prolonged surgical procedures, maintenance doses of 0.01 to 0.015 mg/kg of vecuronium bromide are recommended; after the initial vecuronium bromide injection, the first maintenance dose will generally be required within 25 to 40 minutes. However, clinical criteria should be used to determine the need for maintenance doses.

Since vecuronium bromide lacks clinically important cumulative effects, subsequent maintenance doses, if required, may be administered at relatively regular intervals for each patient, ranging approximately from 12 to 15 minutes under balanced anesthesia, slightly longer under inhalation agents. (If less frequent administration is desired, higher maintenance doses may be administered.)

Should there be reason for the selection of larger doses in individual patients, initial doses ranging from 0.15 mg/kg up to 0.28 mg/kg have been administered during surgery under halothane anesthesia without ill effects to the cardiovascular system being noted as long as ventilation is properly maintained (see CLINICAL PHARMACOLOGY-Pharmacokinetics).

Use by Continuous Infusion

After an intubating dose of 80 to 100 mcg/kg, a continuous infusion of 1 mcg/kg/min can be initiated approximately 20 to 40 minutes later. Infusion of vecuronium bromide should be initiated only after early evidence of spontaneous recovery from the bolus dose. Long-term intravenous infusion to support mechanical ventilation in the intensive care unit has not been studied sufficiently to support dosage recommendations. (See PRECAUTIONS, LONG TERM USE IN I.C.U.).

The infusion of vecuronium bromide should be individualized for each patient. The rate of administration should be adjusted according to the patient's twitch response as determined by peripheral nerve stimulation. An initial rate of 1 mcg/kg/min is recommended, with the rate of the infusion adjusted thereafter to maintain a 90% suppression of twitch response. Average infusion rates may range from 0.8 to 1.2 mcg/kg/min.

Inhalation anesthetics, particularly enflurane and isoflurane may enhance the neuromuscular blocking action of nondepolarizing muscle relaxants. In the presence of steady-state concentrations of enflurane or isoflurane, it may be necessary to reduce the rate of infusion 25 to 60 percent, 45 to 60 min after the intubating dose. Under halothane anesthesia it may not be necessary to reduce the rate of infusion.

Spontaneous recovery and reversal of neuromuscular blockade following discontinuation of vecuronium bromide infusion may be expected to proceed at rates comparable to that following a single bolus dose (see CLINICAL PHARMACOLOGY).

Infusion solutions of vecuronium bromide can be prepared by adding vecuronium bromide with an appropriate infusion solution such as Dextrose 5% Injection, Sodium Chloride 0.9% Injection, Dextrose 5% and Sodium Chloride 0.9% Injection, or Lactated Ringer’s Injection.

Unused portions of infusion solutions should be discarded.

Infusion rates of vecuronium bromide can be individualized for each patient using the following table:

Drug Delivery Rate | Infusion Delivery Rate
(mcg/kg/min) | (mL/kg/min)
 | 0.1 mg/mL* | 0.2 mg/mL†
0.7 | 0.007 | 0.0035
0.8 | 0.008 | 0.004
0.9 | 0.009 | 0.0045
1 | 0.01 | 0.005
1.1 | 0.011 | 0.0055
1.2 | 0.012 | 0.006
1.3 | 0.013 | 0.0065

* 10 mg of vecuronium bromide in 100 mL solution

† 20 mg of vecuronium bromide in 100 mL solution

The following table is a guideline for mL/min delivery for a solution of 0.1 mg/mL (10 mg in 100 mL) with an infusion pump.

VECURONIUM BROMIDE INFUSION RATE - mL/min

Amount of Drug; mcg/kg/min | Patient Weight -kg
Amount of Drug; mcg/kg/min | 40 | 50 | 60 | 70 | 80 | 90 | 100
0.7 | 0.28 | 0.35 | 0.42 | 0.49 | 0.56 | 0.63 | 0.7
0.8 | 0.32 | 0.4 | 0.48 | 0.56 | 0.64 | 0.72 | 0.8
0.9 | 0.36 | 0.45 | 0.54 | 0.63 | 0.72 | 0.81 | 0.9
1 | 0.4 | 0.5 | 0.6 | 0.7 | 0.8 | 0.9 | 1
1.1 | 0.44 | 0.55 | 0.66 | 0.77 | 0.88 | 0.99 | 1.1
1.2 | 0.48 | 0.6 | 0.72 | 0.84 | 0.96 | 1.08 | 1.2
1.3 | 0.52 | 0.65 | 0.78 | 0.91 | 1.04 | 1.17 | 1.3

NOTE: If a concentration of 0.2 mg/mL is used (20 mg in 100 mL), the rate should be decreased by one-half.

Use in Pediatrics

Pediatric patients (10 to 16 years of age) have approximately the same dosage requirements (mg/kg) as adults and may be managed the same way. Younger pediatric patients (1 to 10 years of age) may require a slightly higher initial dose and may also require supplementation slightly more often than adults.

Infants under 1 year of age but older than 7 weeks are moderately more sensitive to vecuronium bromide on a mg/kg basis than adults and take about 1.5 times as long to recover. See also subsection of PRECAUTIONS titled PEDIATRIC USE. Information presently available does not permit recommendation on usage in pediatric patients less than 7 weeks of age (see PRECAUTIONS-PEDIATRIC USE). There are insufficient data concerning continuous infusion of vecuronium in pediatric patients, therefore, no dosing recommendations can be made.

COMPATIBILITY

Vecuronium bromide is compatible in solution with:

Sodium Chloride 0.9% Injection

Dextrose 5% Injection

Sterile Water for Injection

Dextrose 5% in Sodium Chloride 0.9% Injection

Lactated Ringer’s Injection

Use within 24 hours of mixing with the above solutions.

Vecuronium bromide is also compatible in solution with: bacteriostatic water for injection (NOT FOR USE IN NEWBORNS) Use within 5 days of mixing with the above solution.

Reconstituted vecuronium bromide, which has an acid pH, should not be mixed with alkaline solutions (e.g., barbiturate solutions such as thiopental) in the same syringe or administered simultaneously during intravenous infusion through the same needle or through the same intravenous line.

After Reconstitution

See DOSAGE AND ADMINISTRATION-COMPATIBILITY for diluents compatible with Vecuronium Bromide for Injection.

Single Dose Use: When reconstituted with compatible IV solutions not containing an antimicrobial preservative (e.g., sterile water for injection), refrigerate and use within 24 hours. Discard unused portion.

Multi Dose Use: (NOT FOR USE IN NEWBORNS.) When reconstituted with bacteriostatic water for injection, use within 5 days. The reconstituted solution may be stored at room temperature or refrigerated.

Parenteral drug products should be inspected visually for particulate matter and discoloration prior to administration whenever solution and container permit.

Risk of Medication Errors

Accidental administration of neuromuscular blocking agents may be fatal. Store vecuronium bromide for injection with the cap and ferrule intact and in a manner that minimizes the possibility of selecting the wrong product.

HOW SUPPLIED

Vecuronium Bromide for Injection is supplied as follows:

 | NDC | Packaged
10 mg vecuronium bromide | 81565-206-02 | Box of 10 vials

Store dry powder at 20° to 25°C (68° to 77°F) [see USP Controlled Room Temperature]. Protect from light. Retain in carton until time of use.

Manufactured by:

Hikma Farmacêutica (Portugal) S.A.

Estrada do Rio da Mó, 8, 8A e 8B – Fervença – 2705-906 Terrugem, SNT, Portugal

Distributed by:

Phlow Corporation

Richmond, VA 23224

Revised: November 2023

PIN627-PHL/2

Principal Display Panel

NDC 81565-206-01 Rx only

Vecuronium Bromide for Injection

10 mg* per vial

*1 mg/mL

when reconstituted to 10mL

WARNING: Paralyzing Agent.

For Intravenous use ONLY

Principal Display Panel

NDC 81565-206-02 Rx only

Vecuronium Bromide for Injection

10 mg* per vial

*1 mg/mL when reconstituted to 10mL

For Intravenous use ONLY

10 x 10 mg Single Dose Vials

WARNING: Paralyzing Agent. Lyophilized powder - Sterile